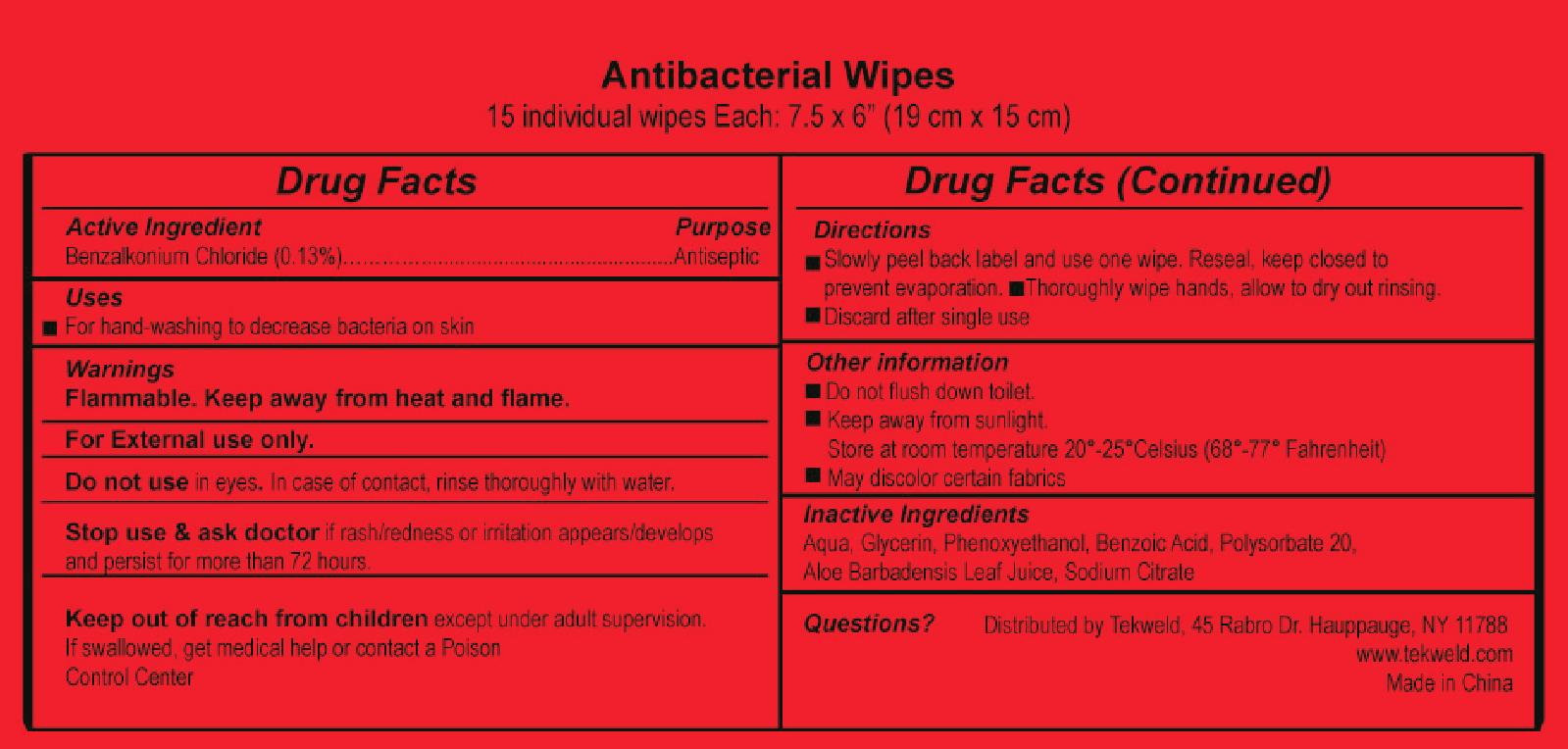 DRUG LABEL: HAND SANITIZER WIPES
NDC: 71766-003 | Form: GEL
Manufacturer: Hangzhou Linkeweier Daily Chemicals Co., Ltd.
Category: otc | Type: HUMAN OTC DRUG LABEL
Date: 20190226

ACTIVE INGREDIENTS: BENZALKONIUM CHLORIDE 0.13 g/100 1
INACTIVE INGREDIENTS: SODIUM CITRATE; WATER; ALOE VERA LEAF; GLYCERIN; PHENOXYETHANOL; BENZOIC ACID; POLYSORBATE 20

Antibacterial Wet Wipes 15 in 1 pack 71766-003

Active Ingredient

benzalkonium chloride 0.13%

Purpose

Antimicrobial

Use

for hand sanitizing to decrease bacteria on the skin.

Warning

Flammable. Keep away from heat and flame.

For External use only.

Do not use in eyes. In case of contact, rinse thoroughly with water.

Stop use & ask doctor if rash/redness or irritation appears/develops

and persist for more than 72 hours.

KEEP OUT OF REACH OF CHILDREN

Keep out of reach from children except under adult supervision.

If swallowed, get medical help or contact a Poison Control Center

Directions

Slowly peel back label and use one wipe. Reseal, keep closed to

prevent evaporation. Thoroughly wipe hands, allow to dry out rinsing.

Discard after single use

Other information

Do not flush down toilet.

Keep away from sunlight.

Store at room temperature 20°-25°Celsius (68°-77° Fahrenheit)

May discolor certain fabrics

INACTIVE INGREDIENT

Aqua, Glycerin, Phenoxyethanol, Benzoic Acid, Polysorbate 20,

Aloe Barbadensis Leaf Juice, Sodium Citrate